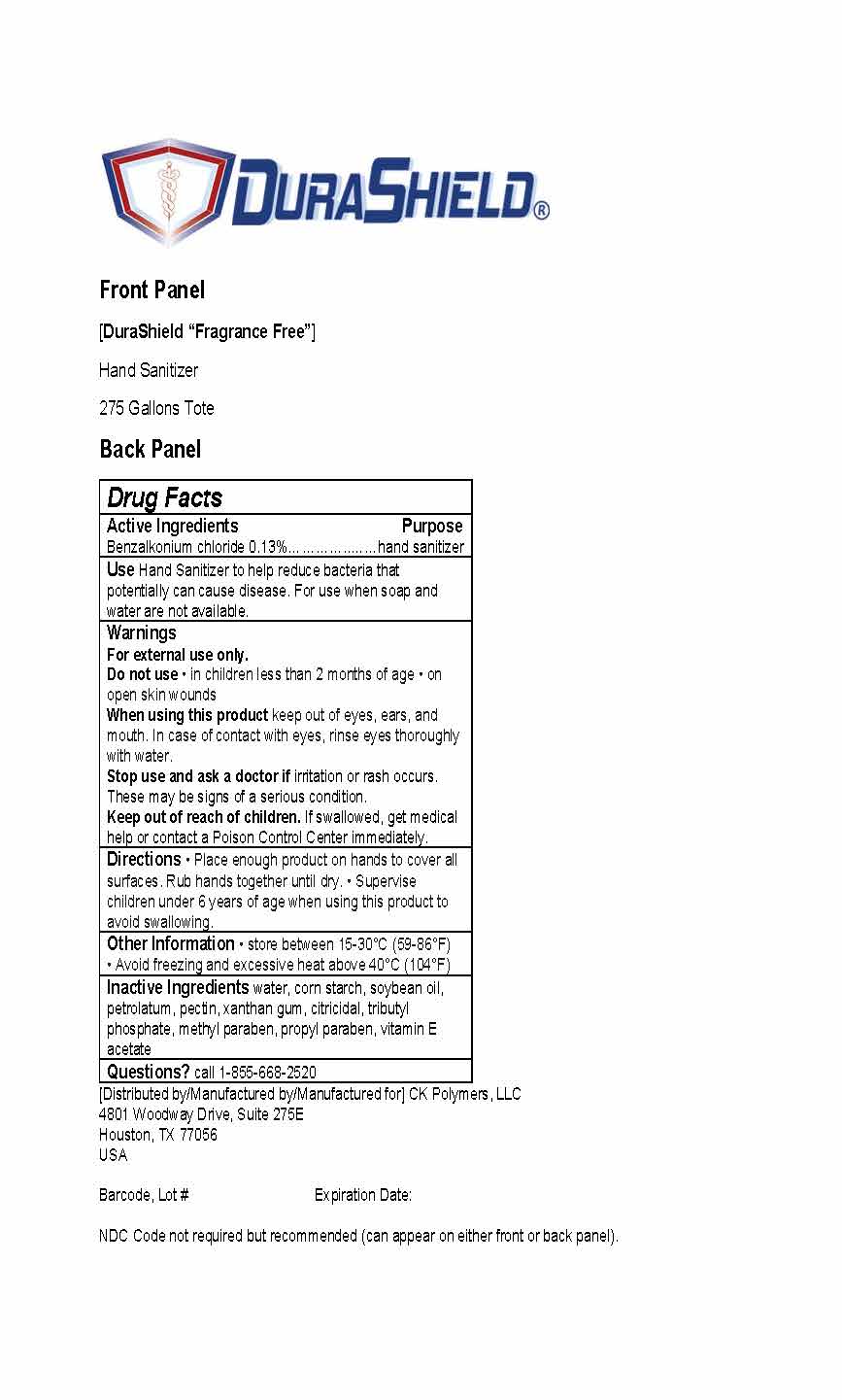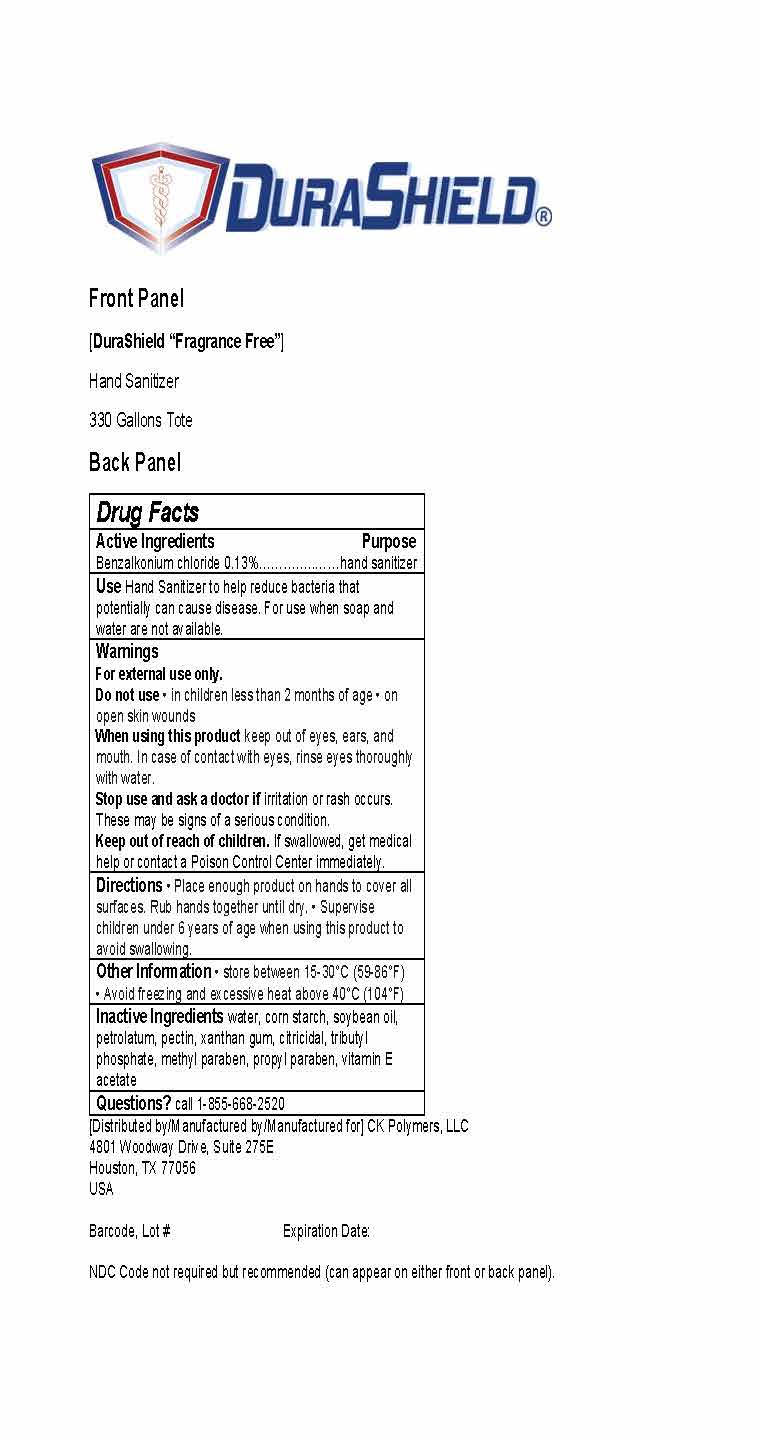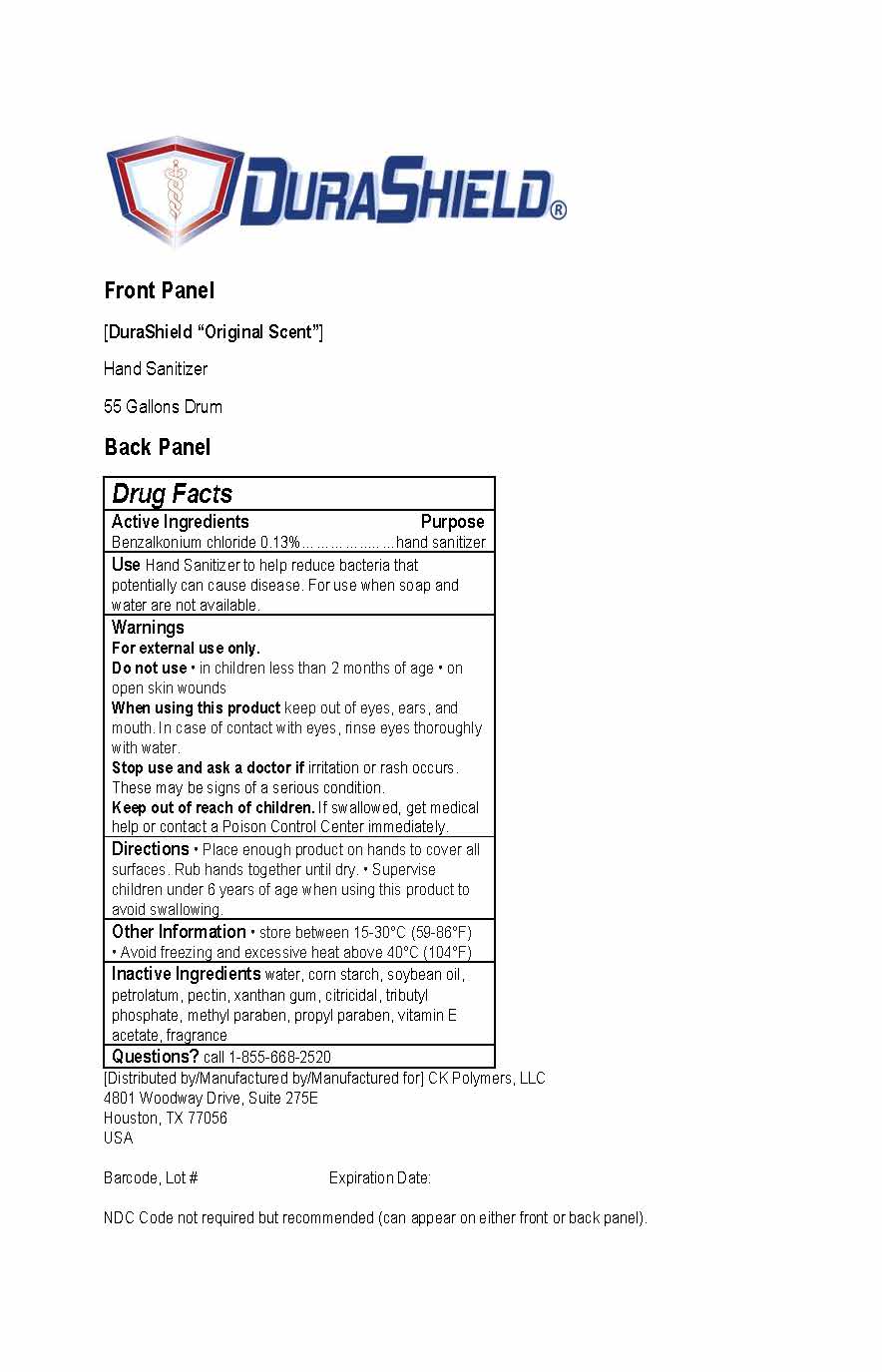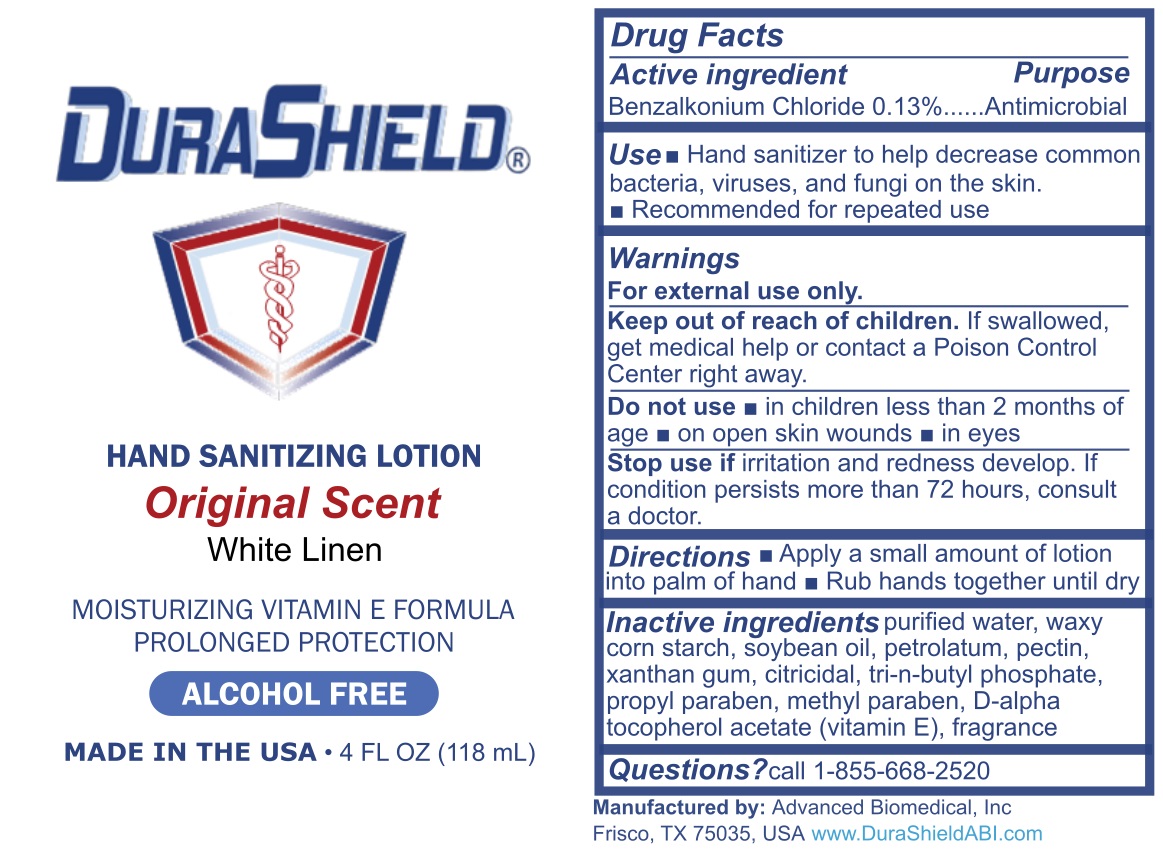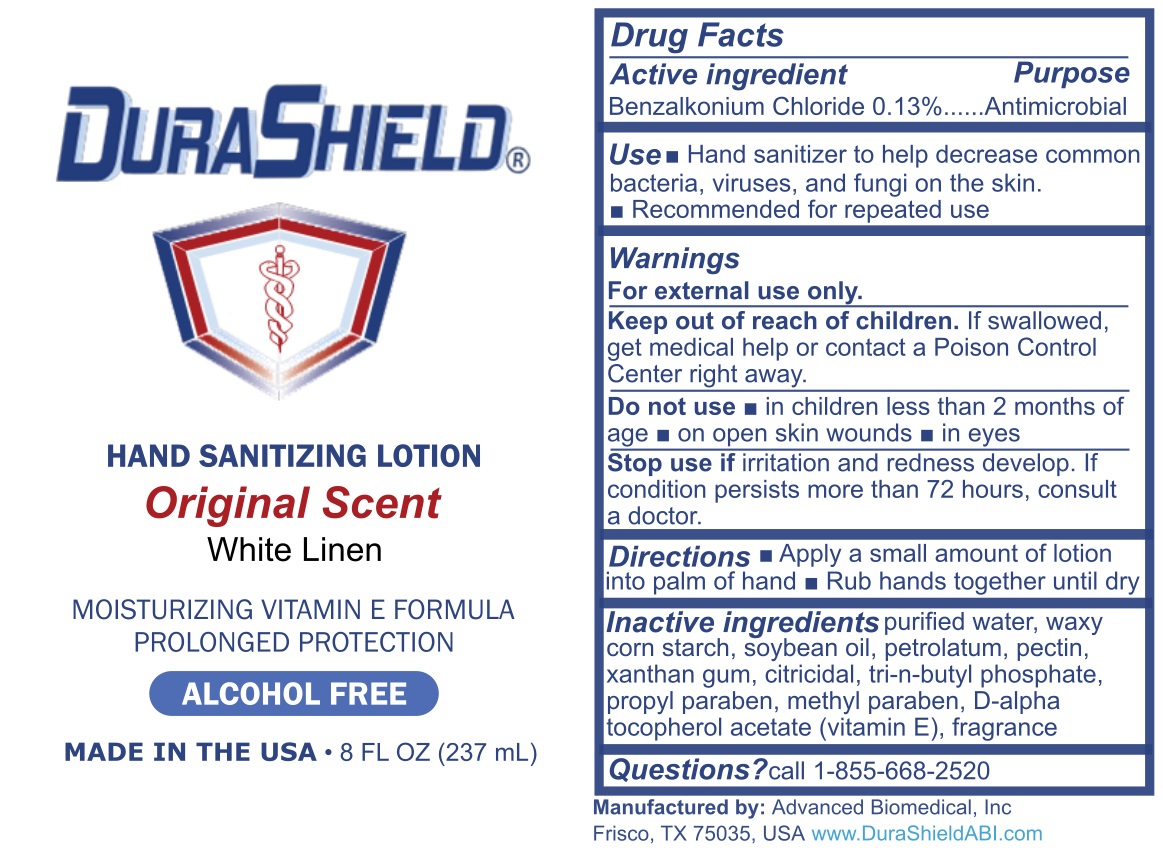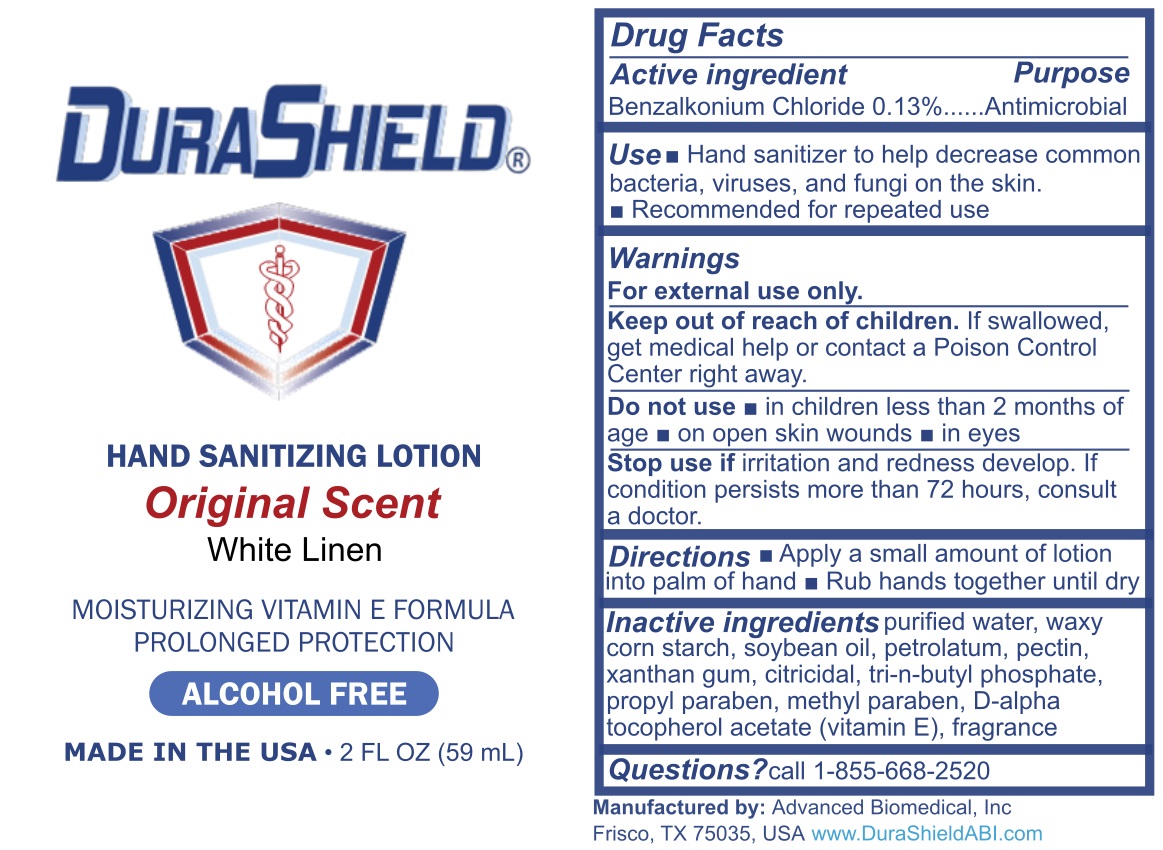 DRUG LABEL: DuraShield Original Scent Hand Sanitizer
NDC: 78235-011 | Form: LOTION
Manufacturer: CK Polymers LLC
Category: otc | Type: HUMAN OTC DRUG LABEL
Date: 20220420

ACTIVE INGREDIENTS: BENZALKONIUM CHLORIDE 1.3 mg/1 mL
INACTIVE INGREDIENTS: WATER; CORN STARCH 3-E-DODECENYL SUCCINIC ANHYDRIDE MODIFIED; SOYBEAN OIL; PETROLATUM; PECTIN; XANTHAN GUM; GRAPEFRUIT SEED OIL; TRIBUTYL PHOSPHITE; METHYLPARABEN; PROPYLPARABEN; ALPHA-TOCOPHEROL ACETATE; BENZYL BENZOATE; HEXAMETHYLINDANOPYRAN; TETRAMETHYL ACETYLOCTAHYDRONAPHTHALENES; .ALPHA.-ISOBUTYLPHENETHYL ALCOHOL; BENZYL ACETATE; METHYL-.ALPHA.-IONONE; BENZYL SALICYLATE; ISOMETHYL-.ALPHA.-IONONE; BUTYLPHENYL METHYLPROPIONAL; NEROL; GERANIOL; ISOAMYL SALICYLATE; HYDROXYISOHEXYL 3-CYCLOHEXENE CARBOXALDEHYDE; CINNAMON LEAF OIL

DuraShield® Original Scent

DuraShield® Original Scent

Active Ingredients

Active Ingredients: Benzalkonium chloride 0.13%

Purpose

Purpose: hand sanitizer

Use

Hand Sanitizer to help reduce bacteria that potentially can cause disease. For use when soap and water are not available.

Warnings

For external use only.

Do not use in children less than 2 months of age or an open skin wounds.

When using this product keep out of eyes, ears, and mouth. In case of contact with eyes, rinse eyes thouroughly with water.

Stop use and ask a doctor if irritation or rash occurs. These may be signs of a serious condition.

Keep out of reach of children. If swallowed, get medical help or contact a Poison Control Center immediately.

Directions

Place enough product on hands to cover all surfaces. Rub hands together until dry. Supervise children under 6 years of age when using this product to avoid swallowing.

Other Information

Store between 15-30°C (59-86°F)

Avoid freezing and excessive heat above 40°C (104°F)

Inactive Ingredients

water, corn starch, soybean oil, petrolatum, pectin, xanthan gum, citricidal, tributyl phosphate, methyl paraben, propyl paraben, vitamin E acetate, white linen fragrance